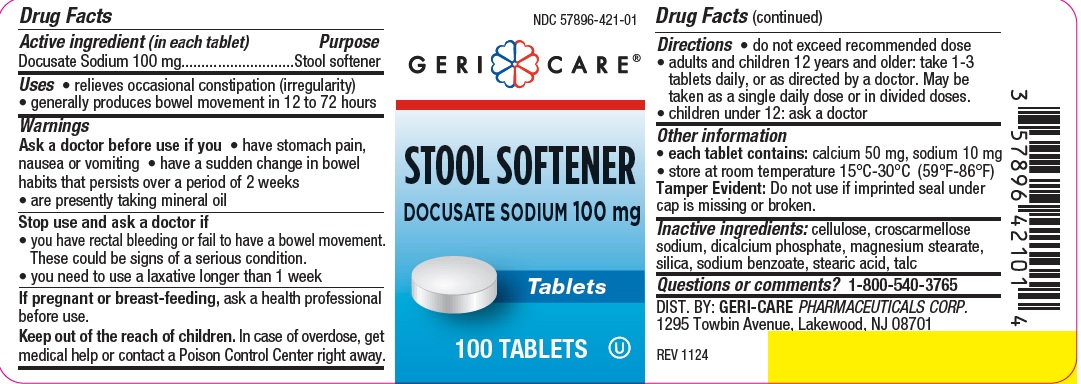 DRUG LABEL: STOOL SOFTENER
NDC: 57896-421 | Form: TABLET
Manufacturer: Geri-Care Pharmaceuticals, Corp
Category: otc | Type: HUMAN OTC DRUG LABEL
Date: 20241216

ACTIVE INGREDIENTS: DOCUSATE SODIUM 100 mg/1 1
INACTIVE INGREDIENTS: SODIUM BENZOATE; STEARIC ACID; CROSCARMELLOSE SODIUM; MICROCRYSTALLINE CELLULOSE; ANHYDROUS DIBASIC CALCIUM PHOSPHATE; MAGNESIUM STEARATE; SILICON DIOXIDE; TALC

Gericare 421

Active ingredient

Docusate Sodium 100 mg

Purpose

Stool Softener

Uses

- relieves occasional constipation (irregularity)
- generally produces bowel movement in 12 to 72 hours

Warnings

Ask a doctor before use if you

- have stomach pain, nausea or vomiting
- have a sudden change in bowel habits that persists over a period of 2 weeks
- are presently taking mineral oil

Stop use and ask a doctor if

- you need to use a laxative longer than 1 week
- you have rectal bleeding or fail to have a bowel movement. These could be signs of a serious condition.

If pregnant or breast-feeding, ask a health professional before use.

Keep out of reach of children

Keep out of the reach of children. In case of overdose, get medical help or contact a Poison Control Center right away.

Directions

- do not exceed recommended dose
- adults and children 12 years and older: take 1-3 tablets daily, or as directed by a doctor. May be taken as a single daily dose or in divided doses.
- children under 12: ask a doctor

Other information

- each tablet contains: calcium 50 mg, sodium 10 mg
- store at room temperature 15°C-30°C (59°F-86°F)
- Tamper Evident: Do not use if imprinted seal under cap is missing or broken

Inactive ingredients

cellulose, croscarmellose sodium, dicalcium phosphate, magnesium stearate, silica, sodium benzoate, stearic acid, talc

Questions or comments?

1-800-540-3765